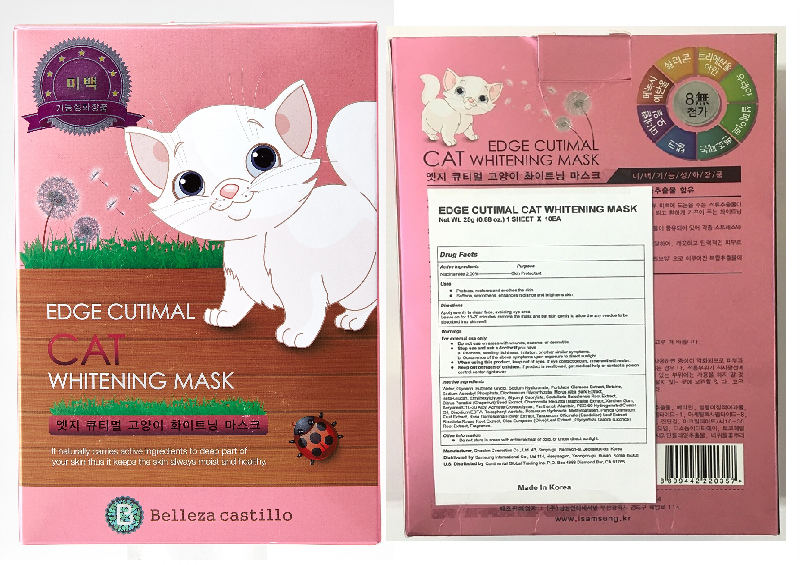 DRUG LABEL: Edge Cutimal Cat Whitening Mask
NDC: 70889-100 | Form: PATCH
Manufacturer: Oneskin Cosmetics Co., Ltd.
Category: otc | Type: HUMAN OTC DRUG LABEL
Date: 20200317

ACTIVE INGREDIENTS: NIACINAMIDE 0.5 g/25 g
INACTIVE INGREDIENTS: SODIUM ASCORBYL PHOSPHATE; HYALURONATE SODIUM; PORTULACA OLERACEA WHOLE; BETAINE; GLYCYRRHIZA GLABRA; METHYLPARABEN; PUNICA GRANATUM WHOLE; TARAXACUM OFFICINALE LEAF; WATER; GLYCERIN; BUTYLENE GLYCOL; GLYCERYL CAPRYLATE/CAPRATE; CITRUS PARADISI SEED; MATRICARIA CHAMOMILLA WHOLE; XANTHAN GUM; ROSA DAMASCENA FLOWERING TOP; EDETATE DISODIUM; ALLANTOIN; PEG-60 HYDROGENATED CASTOR OIL; GLYCYRRHIZINATE DIPOTASSIUM; MORUS ALBA BARK; ETHYLHEXYLGLYCERIN; SCUTELLARIA BAICALENSIS ROOT; PANTHENOL; .ALPHA.-TOCOPHEROL ACETATE; POTASSIUM HYDROXIDE; RHODIOLA ROSEA ROOT; OLEA EUROPAEA LEAF

ACTIVE INGREDIENT

Niacinamide 2.00%

PURPOSE

Skin Protectant

INDICATIONS AND USAGE

- Protects, restores and soothes the skin
- Softens, smoothens, enhances radiance and brightens skin

DOSAGE AND ADMINISTRATION

Apply evenly to clean face, avoiding eye area.

Leave on for 15-20 minutes, remove the mask and pat skin gently to allow the any residue to be absorbed into skin well.

WARNINGS

For external use only

- Do not use on areas with wounds, eczema, or dermatitis.
- Stop use and ask a doctor if you have

a. Redness, swelling, itchiness, irritation, or other similar symptoms.
b. Occurrence of the above symptoms upon exposure to direct sunlight.

- When using this product, keep out of eyes. If eye contact occurs, rinse well with water.

Keep out of reach of children. If product is swallowed, get medical help or contact a poison control center right away.

INACTIVE INGREDIENT

Water, Glycerin, Butylene Glycol, Sodium Hyaluronate, Portulaca Oleracea Extract, Betaine, Sodium Ascorbyl Phosphate, ipotassium Glycyrrhizate, Morus Alba Bark Extract, Beta-Glucan, Ethylhexylglycerin, Glyceryl Caprylate, Scutellaria Baicalensis Root Extract, Citrus Paradisi (Grapefruit) Seed Extract, Chamomilla Recutita (Matricaria) Extract, Xanthan Gum, Acrylates/C10-30 Alkyl Acrylate Crosspolymer, Panthenol, Allantoin, PEG-60 Hydrogenated Castor Oil, Disodium EDTA, Tocopheryl Acetate, Potassium Hydroxide, Methylparaben, Punica Granatum Fruit Extract, Rosa Damascena Flower Extract, Taraxacum Officinale (Dandelion) Leaf Extract, Rhodiola Rosea Root Extract, Olea Europaea (Olive) Leaf Extract , Glycyrrhiza Glabra (Licorice) Root Extract, Fragrance.

OTHER SAFETY INFORMATION

Do not store in areas with extreme heat or cold, or under direct sunlight.